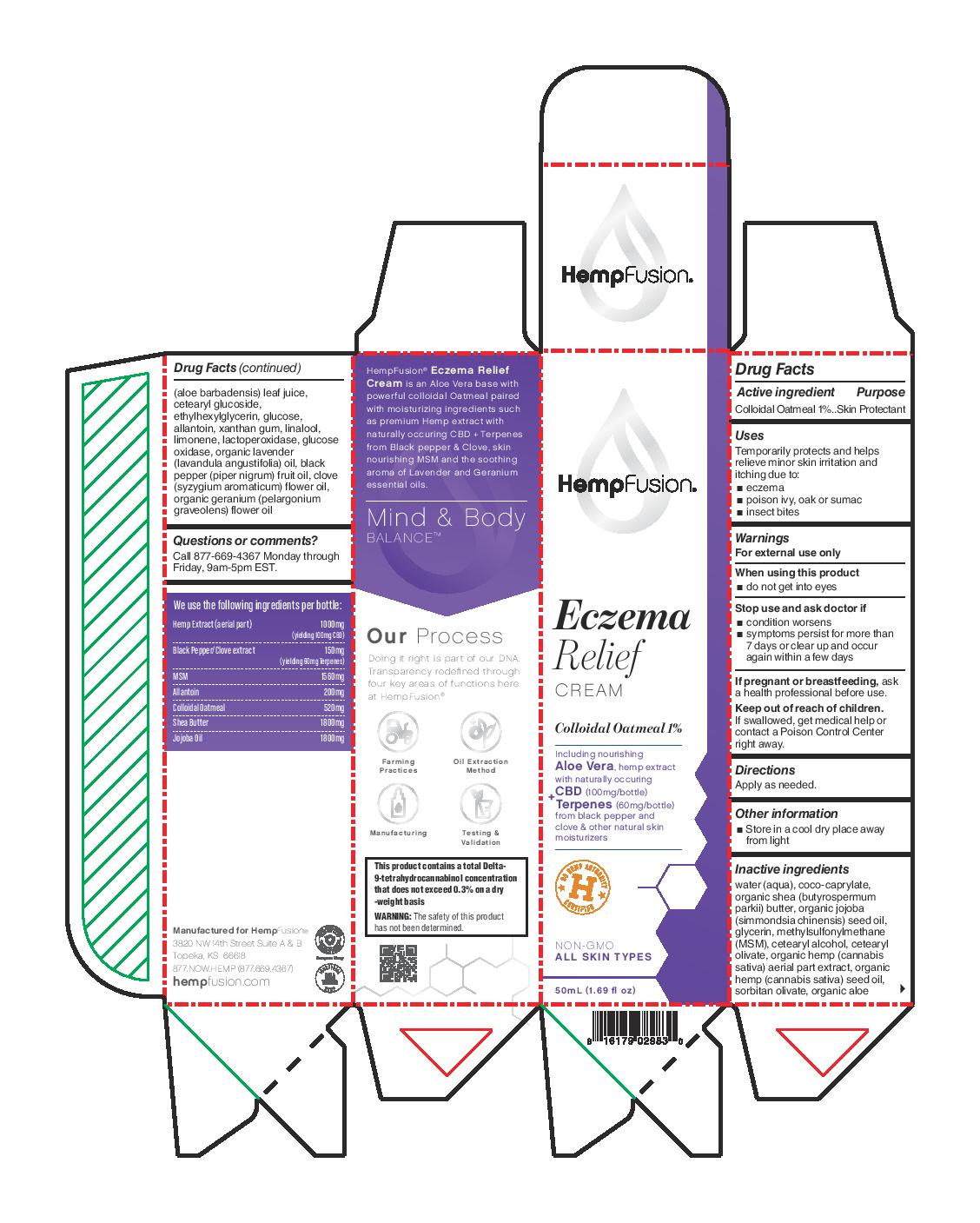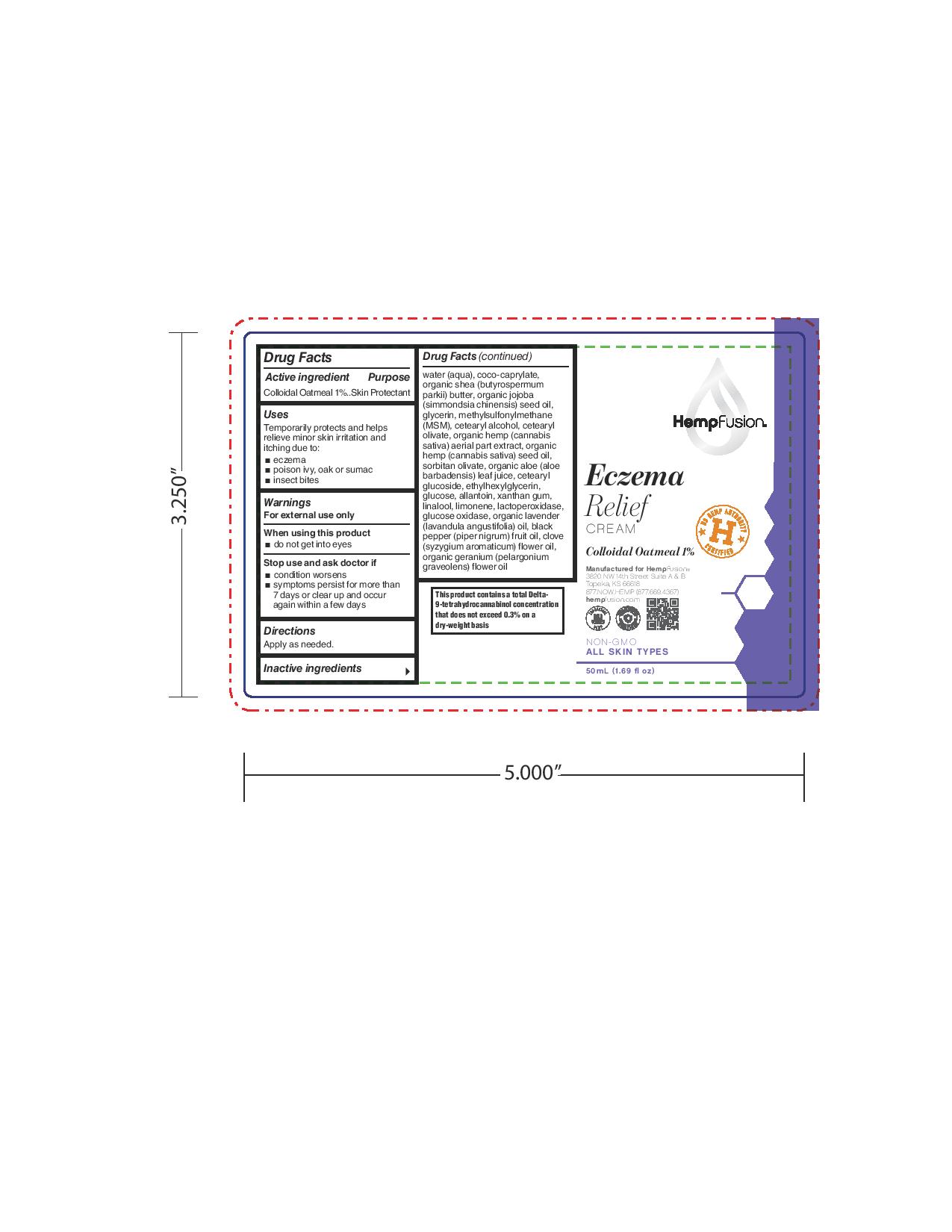 DRUG LABEL: Eczema Relief Cream
NDC: 73672-983 | Form: CREAM
Manufacturer: HEMPFUSION, INC.
Category: otc | Type: HUMAN OTC DRUG LABEL
Date: 20210317

ACTIVE INGREDIENTS: OATMEAL 10 mg/1 mL
INACTIVE INGREDIENTS: LIMONENE, (+)-; ALOE; ETHYLHEXYLGLYCERIN; ALLANTOIN; LINALOOL, (+/-)-; MYELOPEROXIDASE; GLUCOSE OXIDASE; LAVENDER OIL; CETOSTEARYL ALCOHOL; SORBITAN OLIVATE; SHEA BUTTER; GLYCERIN; WATER; COCO-CAPRYLATE; JOJOBA OIL; DIMETHYL SULFONE; CETEARYL OLIVATE; HEMP; CANNABIS SATIVA SEED OIL; CETEARYL GLUCOSIDE; ANHYDROUS DEXTROSE; XANTHAN GUM; BLACK PEPPER OIL; CLOVE OIL; PELARGONIUM GRAVEOLENS FLOWER OIL

Eczema Relief Cream

Active ingredient

Colloidal Oatmeal 1%

Purpose

Colloidal Oatmeal 1%...Skin Protectant

Uses

Temporarily protects and helps relieve minor skin irritation and itching due to:

- eczema
- poison ivy, oak or sumac
- insect bites

Warnings

For external use only

When using this product

- do not get into eyes

Stop use and ask doctor if

- condition worsens
- symptoms persist for more than 7 days or clear up and occur again within a few days

PREGNANCY OR BREAST FEEDING

If pregnant or breastfeeding, ask a health professional before use.

KEEP OUT OF REACH OF CHILDREN

Keep out of reacho f children. If swallowed, get medical help or contact a Poison Control Center right away.

Directions

Apply as needed.

Other information

- Store in a cool dry place away from light

Inactive ingredients

water (aqua), coco-caprylate, organic shea (butyrospermum parkii) butter, organic jojoba (simmondsia chinensis) seed oil, glycerin, methylsulfonylmethane (MSM), cetearyl alcohol, cetearyl olivate, organic hemp (cannabis sativa) aerial part extract, organic hemp (cannabis sativa) seed oil, sorbitan olivate, organic aloe (aloe barbadensis) leaf juice, cetearyl glucoside, ethylhexylglycerin, glucose,

allantoin, xanthan gum, linalool, limonene, lactoperoxidase, glucose oxidase, organic lavender (lavandula angustifolia) oil, black pepper (piper nigrum) fruit oil, clove (syzygium aromaticum) flower oil, organic geranium (pelargonium graveolens) flower oi

Questions or comments?

Call 877-669-4367 Monday through Friday, 9am-5pm EST.

Principal Display Panel

HempFusion

Eczema

Relief

CREAM

Colloidal Oatmeal 1%

Including nourishing Aloe Vera, hemp extract with naturally occuring CBD (100mg/bottle) + Terpenes (60mg/bottle) from black pepper and clove & other natural skin moisturizers

U.S. Hemp Authority H Certified

NON-GMO

ALL SKIN TYPES

50mL (1.69 fl oz)